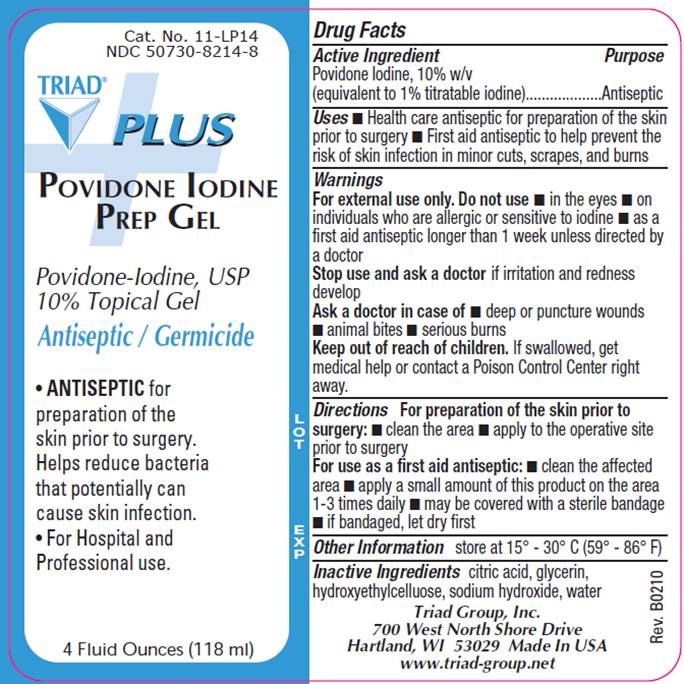 DRUG LABEL: Povidone Iodine Plus
NDC: 50730-8214 | Form: GEL
Manufacturer: H and P Industries, Inc. dba Triad Group
Category: otc | Type: HUMAN OTC DRUG LABEL
Date: 20100422

ACTIVE INGREDIENTS: povidone-iodine 0.10 g/1 mL
INACTIVE INGREDIENTS: CITRIC ACID MONOHYDRATE; GLYCERIN; HYDROXYETHYL CELLULOSE (2000 CPS AT 1%); SODIUM HYDROXIDE; WATER

DRUG FACTS

ACTIVE INGREDIENT

Povidone Iodine USP 10% (equivalent to 1% titratable iodine)

PURPOSE

Antiseptic

USES

- Health care antiseptic for preparation of the skin prior to surgery
- First aid antiseptic to help prevent infection in minor cuts, scrapes and burns

WARNINGS

For external use only.

Do not use

- in the eyes
- on individuals who are allergic or sensitive to iodine
- as a first aid antiseptic longer than 1 week unless directed by a doctor

Ask a doctor in case of

- deep or puncture wounds
- animal bites
- serious burns

Stop use and ask a doctor if

- irritation and redness develop

Keep out of reach of children

If swallowed, get medical help or contact a Poison Control Center right away.

DIRECTIONS

For preparation of the skin prior to surgery

- apply to the operative site prior to surgery

As a first aid antiseptic

- clean the affected area
- apply a small amount of this product to the area 1-3 times daily
- may be covered with a sterile bandage
- if bandaged, let dry first

OTHER INFORMATION

Store at 15° - 30° C (59° - 86° F)

INACTIVE INGREDIENTS

citric acid, glycerin, hydroxyethylcellulose, sodium hydroxide, water

PACKAGE INFORMATION

Cat. No. 11-LP14
NDC 50730-8214-8
TRIAD Plus
POVIDONE IODINE
PREP GEL
Povidone Iodine, USP
10% Topical Gel

- ANTISEPTIC for preparation of the skin prior to surgery. Helps reduce bacteria that potentially can cause skin infection.
- For Hospital and Professional use.

4 Fluid Ounces (118 ml)
Triad Group, Inc.
700 West North Shore Drive
Hartland, WI 53029 Made In USA
www.triad-group.net